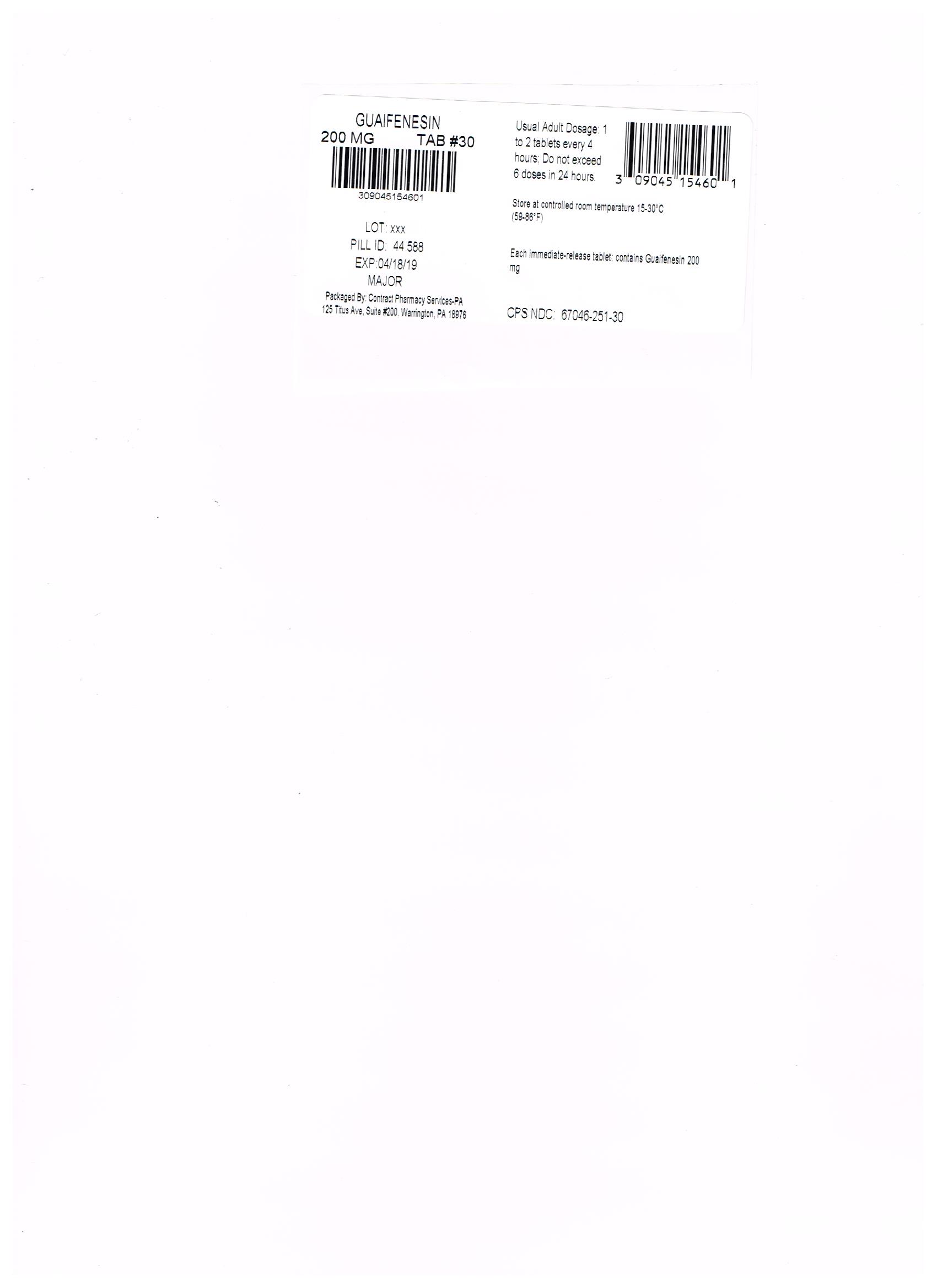 DRUG LABEL: Guaifenesin
NDC: 67046-251 | Form: TABLET
Manufacturer: Contract Pharmacy Services-PA
Category: otc | Type: HUMAN OTC DRUG LABEL
Date: 20180419

ACTIVE INGREDIENTS: GUAIFENESIN 200 mg/1 1
INACTIVE INGREDIENTS: SILICON DIOXIDE

HIGHLIGHTS OF PRESCRIBING INFORMATION

Guaifenesin 200mg USP 251 "These highlights do not include all the information needed to use" "see full prescribing information for" "Initial U.S. Approval"

DOSAGE AND ADMINISTRATION

Directions do not exceed 6 doses in 24 hours take with a full glass of water adults and children 12 yearsof age and over 1 to 2 tablets every4 hours children 6 to under 12 yearsof age ½ to 1 tablet every4 hours children under 6 years of age consult a physician

INDICATIONS AND USAGE

helps loosen phlegm (mucus) and thin bronchial secretions to rid the bronchial passageways of bothersome mucus and make coughs more productive

FULL PRESCRIBING INFORMATION

PATIENT INFORMATION

Major 44-588 Major Pharmaceuticals LNK International, Inc. LNK International, Inc. LNK International, Inc. LNK International, Inc. Guaifenesin Guaifenesin GUAIFENESIN GUAIFENESIN MAGNESIUM STEARATE MALTODEXTRIN CELLULOSE, MICROCRYSTALLINE POVIDONE STEARIC ACID FD&C RED NO. 40 SILICON DIOXIDE dark 44;588 Active ingredient (in each immediate-release tablet) Guaifenesin 200 mg Purpose Expectorant Uses helps loosen phlegm (mucus) and thin bronchial secretions to rid the bronchial passageways of bothersome mucus and make coughs more productive Warnings Ask a doctor before use if you have persistent or chronic cough such as occurs with smoking, asthma, chronic bronchitis, or emphysema cough accompanied by too much phlegm (mucus) Stop use and ask a doctor if cough lasts more than 7 days, comes back, or occurs with fever, rash, or persistent headache. These could be signs of a serious illness. If pregnant or breast-feeding, ask a health professional before use. Keep out of reach of children. In case of overdose, get medical help or contact a Poison Control Center right away. Directions do not exceed 6 doses in 24 hours take with a full glass of water adults and children 12 yearsof age and over 1 to 2 tablets every4 hours children 6 to under 12 yearsof age ½ to 1 tablet every4 hours children under 6 years of age consult a physician Other information store at 25ºC (77ºF); excursions permitted between 15º-30ºC (59º-86ºF) use by expiration date on package Inactive ingredients FD&C red #40 aluminum lake, magnesium stearate, maltodextrin, microcrystalline cellulose, povidone, silica gel, sodium starch glycolate, stearic acid Questions or comments? (800) 616-2471 Principal Display Panel NDC 0904-5154-60 MAJOR® GUAIFENESIN TABLETSGuaifenesin 200 mg Expectorant Relieves Chest Congestion Thins and Loosens Mucus 100 Tablets Immediate Release 50844 REV0812B58812Distributed by MAJOR® PHARMACEUTICALS 31778 Enterprise Drive, Livonia, MI 48150 USARe-Order No. 238163 M-17 Rev. 04/13 TAMPER EVIDENT: DO NOT USE IF IMPRINTED SAFETY SEAL UNDER CAP IS BROKEN OR MISSING Major 44-588 Major 44-588 REPACKAGED BY: COUPLER ENTERPRISES INC. NDJA 4/19/18

Keep out of reach of children. In case of overdose, get medical help or contact a Poison Control Center right away. Directions do not exceed 6 doses in 24 hours take with a full glass of water adults and children 12 yearsof age and over 1 to 2 tablets every4 hours children 6 to under 12 yearsof age ½ to 1 tablet every4 hours children under 6 years of age consult a physician

WARNINGS

Warnings Ask a doctor before use if you have persistent or chronic cough such as occurs with smoking, asthma, chronic bronchitis, or emphysema cough accompanied by too much phlegm (mucus) Stop use and ask a doctor if cough lasts more than 7 days, comes back, or occurs with fever, rash, or persistent headache. These could be signs of a serious illness. If pregnant or breast-feeding, ask a health professional before use

INACTIVE INGREDIENT

Inactive ingredients FD&C red #40 aluminum lake, magnesium stearate, maltodextrin, microcrystalline cellulose, povidone, silica gel, sodium starch glycolate, stearic acid

ACTIVE INGREDIENT

Guaifenesin 200 mg

PURPOSE

Expectorant